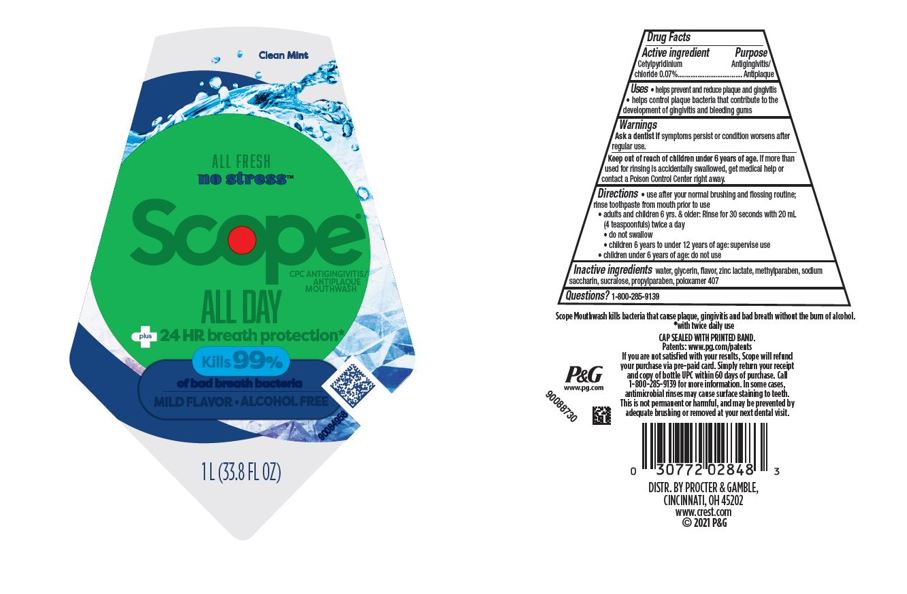 DRUG LABEL: Scope All Day CPC Antigingivitis/Antiplaque Mouthwash

NDC: 69423-856 | Form: RINSE
Manufacturer: The Procter & Gamble Manufacturing Company
Category: otc | Type: HUMAN OTC DRUG LABEL
Date: 20250731

ACTIVE INGREDIENTS: CETYLPYRIDINIUM CHLORIDE 0.07 g/1 mL
INACTIVE INGREDIENTS: SACCHARIN SODIUM; WATER; GLYCERIN; METHYLPARABEN; PROPYLPARABEN; POLOXAMER 407; SUCRALOSE; ZINC LACTATE

Scope All Day

Drug Facts

Active ingredient

Cetylpyridinium chloride 0.07%

Purpose

Antigingivitis/Antiplaque

Uses

- helps prevent and reduce plaque and gingivitis
- helps control plaque bacteria that contribute to the development of gingivitis and bleeding gums

Warning

WARNINGS

Ask a dentist if symptoms persist or condition worsens after regular use.

Keep out of reach of children 6 years of age.If more than used for rinsing is accidentally swallowed, get medical help or contact a Poison Control Center right away.

Directions

- use after your normal brushing and flossing routine, rinse toothpaste from mouth prior to use
- adults and children 6 yrs. & older: Rinse for 30 seconds with 20 mL (4 teaspoonfuls) twice a day
- do not swallow
- children 6 years to under 12 years of age: supervise use
- children under 6 years of age: do not use

Questions?

1-800-285-9139

Inactive ingredients

water, glycerin, flavor, zinc lactate, methylparaben, sodium saccharin, sucralose, propylparaben, poloxamer 407

DISTR. BY PROCTER & GAMBLE,

CINCINNATI, OH 45202

Principal Display Panel 1L bottle

Clean Mint

ALL FRESH

no stress™

Scope®

CPC ANTIGINGIVITIS/ANTIPLAQUE MOUTHWASH

ALL DAY

plus 24 HR breath protection*

Kills 99%

of bad breath bacteria

MILD FLAVOR

ALCOHOL FREE

1 L (33.8 FL OZ)